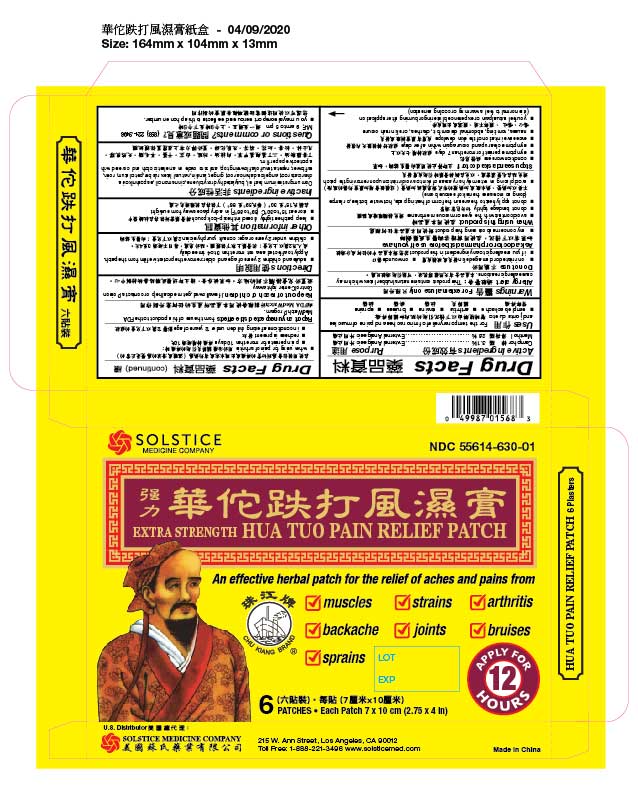 DRUG LABEL: EXTRA STRENGTH HUA TUO PAIN RELIEF
NDC: 55614-630 | Form: PATCH
Manufacturer: MADISON ONE ACME INC
Category: otc | Type: HUMAN OTC DRUG LABEL
Date: 20251110

ACTIVE INGREDIENTS: CAMPHOR (SYNTHETIC) 3.1 g/100 g; MENTHOL 2.6 g/100 g
INACTIVE INGREDIENTS: OCIMUM GRATISSIMUM LEAF OIL; BUTYLATED HYDROXYTOLUENE; CINNAMON OIL; SAPOSHNIKOVIA DIVARICATA ROOT; ANGELICA DAHURICA ROOT; GINGER; LANOLIN; NATURAL LATEX RUBBER; PETROLATUM; ROSIN; SAFFLOWER; NEPETA TENUIFOLIA FLOWERING TOP; ZINC OXIDE

Drug Facts

Active Ingredients
Camphor 3.1%
Menthol 2.6%

Purpose
External Analgesic
External Analgesic

Uses
For the temporary relief of minor aches and pains of muscles and joints due to:
■ simple backache ■ arthritis ■ strains ■ bruises ■ sprains

Warnings
For external use only
Allergy alert: This product contains natural rubber latex which may cause allergic reactions.

Do not use■ on irritated or damaged skin
■ on wounds
■ if you are allergic to any ingredient in this product

Ask a doctor or pharmacist before use if you have
■ any concerns about using this product

When using this product
■ avoid contact with the eyes or mucous membranes
■ do not bandage tightly
■ do not apply heat to the area in the form of heating pads, hot water bottles, or lamps (doing so increases the risk of serious burns)
■ avoid placing on extremely hairy areas of skin to avoid irritation upon removing the patch

Stop use and ask a doctor if
■ condition worsens
■ symptoms persist for more than 7 days
■ symptoms clear up and occur again within a few days
■ excessive irritation of the skin develops
■ nausea, vomiting, abdominal discomfort, diarrhea, or skin rash occurs
■ you feel actual pain or experience blistering or burning after application (it is normal to feel a warming or cooling sensation)
■ when using for pain of arthritis:
■ pain persists for more than 10 days
■ redness is present
■ in conditions affecting children under 12 years of age

ADVERSE REACTIONS

Report any unexpected side effectsfrom the use of this product to the FDA MedWatch Program.

Keep out of reach of children.If swallowed, get medical help or contact a Poison Control Center right away.

Directions
■ adults and children 2 years of age and older: remove the protective film from the patch. Apply to affected area not more than 3 to 4 times daily.
■ children under 2 years of age: consult your physician

Other information
■ keep patches tightly closed in the zip-lock pouch
■ store at 15º to 30º C (59º to 86º F) in a dry place away from sunlight

Inactive ingredients
Ocimum gratissimum leaf oil, butylated hydroxytoluene, cinnamon oil, saposhnikovia divaricata root, angelica dahurica root, ginger, lanolin, natural latex rubber, petrolatum, rosin, safflower, nepeta tenuifolia flowering top, and zinc oxide on an elastic cloth and covered with a protective paper film.

Questions or comments?
(888) 221-3496 M-F 9 am to 5 pm
■ you may also report serious side effects to this phone number

PACKAGE LABEL

EXTRA STRENGTH HUA TUO PAIN RELIEF PATCH

NDC 55614-630-01

An effective herbal patch for the relief of aches and pains from muscles, strains, arthritis, backache, joints, bruises, sprains.

6 Patches
Each Patch 7 x 10 cm (2.75 x 4 in)

Apply for 12 Hours